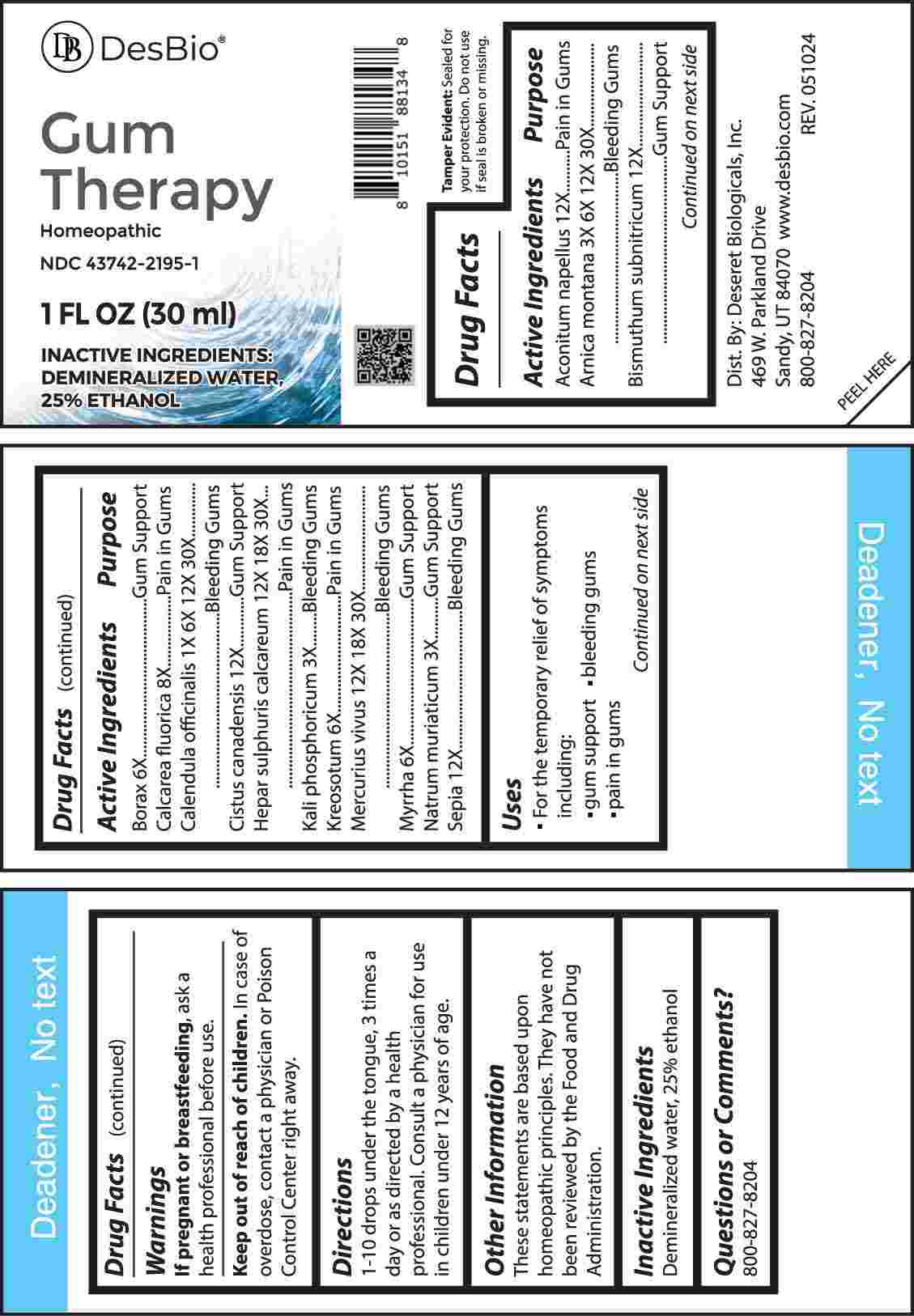 DRUG LABEL: Gum Therapy
NDC: 43742-2195 | Form: LIQUID
Manufacturer: Deseret Biologicals
Category: homeopathic | Type: HUMAN OTC DRUG LABEL
Date: 20240829

ACTIVE INGREDIENTS: ACONITUM NAPELLUS WHOLE 12 [hp_X]/1 mL; ARNICA MONTANA WHOLE 3 [hp_X]/1 mL; BISMUTH SUBNITRATE 12 [hp_X]/1 mL; SODIUM BORATE 6 [hp_X]/1 mL; CALCIUM FLUORIDE 8 [hp_X]/1 mL; CALENDULA OFFICINALIS FLOWERING TOP 1 [hp_X]/1 mL; HELIANTHEMUM CANADENSE 12 [hp_X]/1 mL; CALCIUM SULFIDE 12 [hp_X]/1 mL; DIBASIC POTASSIUM PHOSPHATE 3 [hp_X]/1 mL; WOOD CREOSOTE 6 [hp_X]/1 mL; MERCURY 12 [hp_X]/1 mL; MYRRH 6 [hp_X]/1 mL; SODIUM CHLORIDE 3 [hp_X]/1 mL; SEPIA OFFICINALIS JUICE 12 [hp_X]/1 mL
INACTIVE INGREDIENTS: WATER; ALCOHOL

DRUG FACTS:

ACTIVE INGREDIENTS:

Aconitum Napellus 12X, Arnica Montana 3X, 6X, 12X, 30X, Bismuthum Subnitricum 12X, Borax 6X, Calcarea Fluorica 8X, Calendula Officinalis 1X, 6X, 12X, 30X, Cistus Canadensis 12X, Hepar Sulphuris Calcareum 12X, 18X, 30X, Kali Phosphoricum 3X, Kreosotum 6X, Mercurius Vivus 12X, 18X, 30X, Myrrha 6X, Natrum Muriaticum 3X, Sepia 12X.

PURPOSE:

Aconitum Napellus – Pain in Gums, Arnica Montana – Bleeding Gums, Bismuthum Subnitricum – Gum Support, Borax – Gum Support, Calcarea Fluorica – Pain in Gums, Calendula Officinalis – Bleeding Gums, Cistus Canadensis – Gum Support, Hepar Sulphuris Calcareum – Pain in Gums, Kali Phosphoricum – Bleeding Gums, Kreosotum – Pain in Gums, Mercurius Vivus – Bleeding Gums, Myrrha – Gum Support, Natrum Muriaticum – Gum Support, Sepia – Bleeding Gums

USES:

• For the temporary relief of symptoms including:

• gum support • bleeding gums • pain in gums

These statements are based upon homeopathic principles. They have not been reviewed by the Food and Drug Administration.

WARNINGS:

If pregnant or breast-feeding, ask a health professional before use.

Keep out of reach of children. In case of overdose, contact a physician or Poison Control Center right away.

Tamper Evident: Sealed for your protection. Do not use if seal is broken or missing.

KEEP OUT OF REACH OF CHILDREN:

In case of overdose, contact a physician or Poison Control Center right away.

DIRECTIONS:

1-10 drops under the tongue, 3 times a day or as directed by a health professional. Consult a physician for use in children under 12 years of age.

INACTIVE INGREDIENTS:

Demineralized water, 25% ethanol

QUESTIONS:

Dist. By: Deseret Biologicals, Inc.

469 W. Parkland Drive

Sandy, UT 84070

www.desbio.com

800-827-8204

PACKAGE LABEL DISPLAY:

DesBio

Gum Therapy

Homeopathic
NDC 43742-2195-1
1 FL OZ (30 ml)